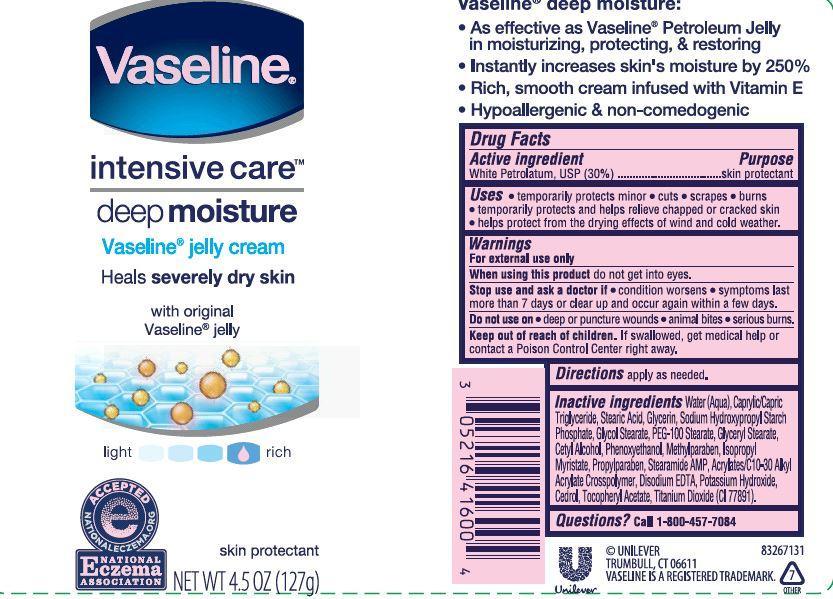 DRUG LABEL: Vaseline
NDC: 64942-1401 | Form: CREAM
Manufacturer: Conopco Inc. d/b/a Unilever
Category: otc | Type: HUMAN OTC DRUG LABEL
Date: 20221206

ACTIVE INGREDIENTS: PETROLATUM 30 g/100 g
INACTIVE INGREDIENTS: METHYLPARABEN; ISOPROPYL MYRISTATE; PROPYLPARABEN; STEARAMIDE AMP; .ALPHA.-TOCOPHEROL ACETATE, D-; POTASSIUM HYDROXIDE; CEDROL; EDETATE DISODIUM; TITANIUM DIOXIDE; WATER; MEDIUM-CHAIN TRIGLYCERIDES; STEARIC ACID; GLYCERIN; GLYCOL STEARATE; PEG-100 STEARATE; GLYCERYL MONOSTEARATE; CETYL ALCOHOL; PHENOXYETHANOL

Vaseline Intensive Care Deep Moisture

Active ingredient

WHITE PETROLATUM USP (30%)

Purpose

skin protectant

INDICATIONS AND USAGE

Uses ●temporarily protects minor ● cuts ● scrapes ● burns

● temporarily protects and helps relieve chapped or cracked skin

● helps protect from the drying effects of wind and cold weather

WARNINGS
For External Use Only

When using this product do not get into eyes.

Stop use and ask a doctor if ● condition worsens ● symptoms last more than 7 days or clear up and occur again within a few days.

Do not use on ● deep or puncture wounds ● animal bites ● serious burns

Keep out of reach of children. If swallowed get medical help or contact a Poison Control Center right away.

DOSAGE AND ADMINISTRATION

Directions apply as needed.

INACTIVE INGREDIENT

Inactive ingredients Water (Aqua), Caprylic/Capric Triglyceride, Stearic Acid, Glycerin, Sodium Hydroxypropyl Starch Phosphate, Glycol Stearate, PEG-100 Stearate, Glyceryl Stearate, Cetyl Alcohol, Phenoxyethanol, Methylparaben, Isopropyl Myristate, Propylparaben, Stearamide AMP, Acrylates/C10-30 Alkyl Acrylate Crosspolymer, Disodium EDTA, Potassium Hydroxide, Cedrol, Tocopheryl Acetate, Titanium Dioxide (CI 77891).

Questions? Call 1-800-457-7084